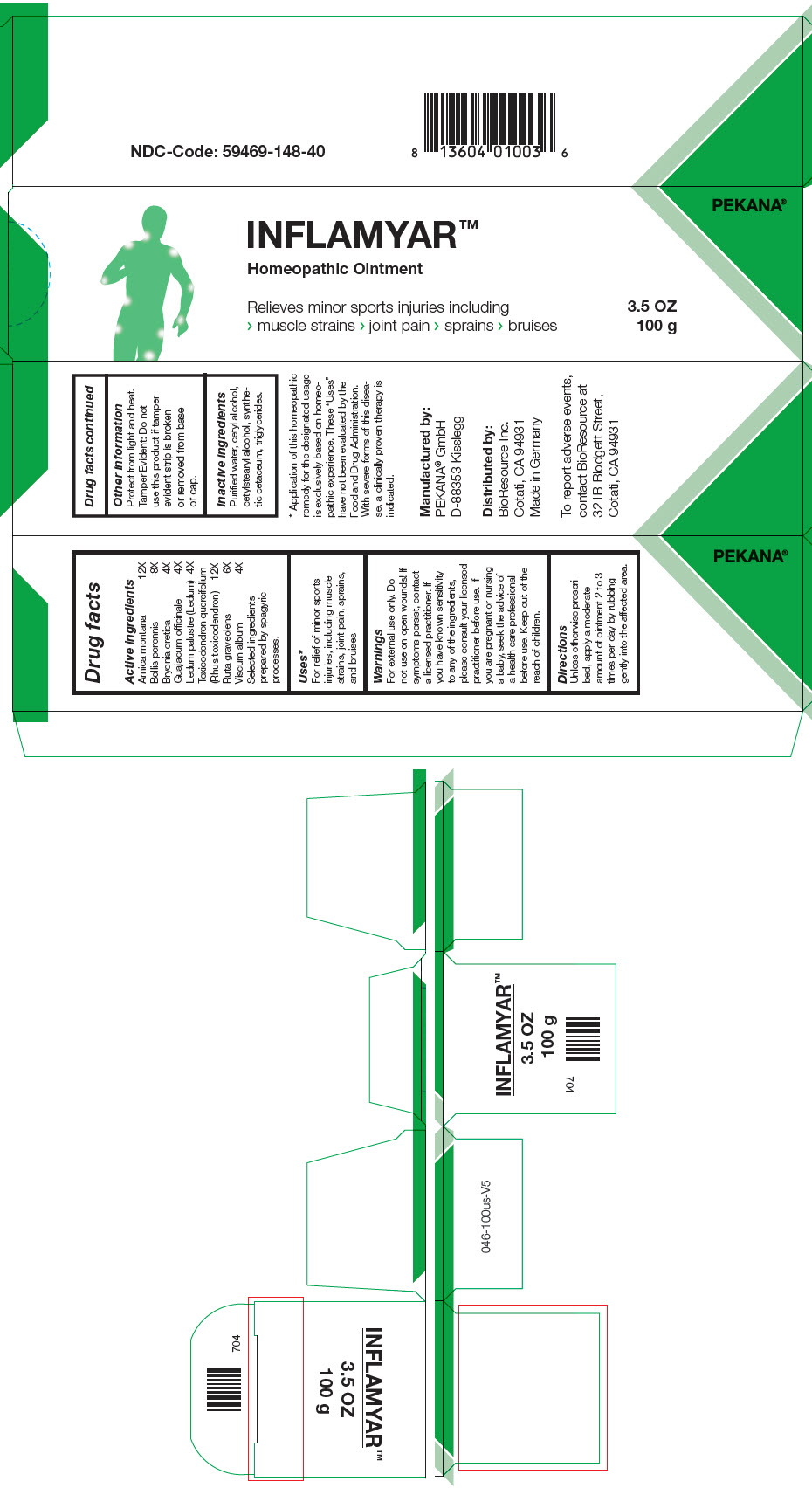 DRUG LABEL: inflamyar
NDC: 59469-148 | Form: OINTMENT
Manufacturer: PEKANA Naturheilmittel GmbH
Category: homeopathic | Type: HUMAN OTC DRUG LABEL
Date: 20221214

ACTIVE INGREDIENTS: Arnica montana Root 12 [hp_X]/100 g; Bryonia Dioica Root 4 [hp_X]/100 g; Guaiacum officinale Resin 4 [hp_X]/100 g; Toxicodendron Pubescens Shoot 12 [hp_X]/100 g; Bellis Perennis Whole 8 [hp_X]/100 g; RHODODENDRON TOMENTOSUM LEAFY TWIG 4 [hp_X]/100 g; Ruta graveolens Flowering Top 6 [hp_X]/100 g; Viscum album Fruiting Top 4 [hp_X]/100 g
INACTIVE INGREDIENTS: Medium-Chain Triglycerides; Cetostearyl Alcohol; Cetyl Alcohol; Spermaceti; Water; Alcohol

INFLAMYAR™

Drug facts

ACTIVE INGREDIENT

PURPOSE

Active ingredients
Arnica montana | 12X
Bellis perennis | 8X
Bryonia cretica | 4X
Guajacum officinale | 4X
Ledum palustre (Ledum) | 4X
Toxicodendron quercifolium (Rhus toxicodendron) | 12X
Ruta graveolens | 6X
Viscum album | 4X

Selected ingredients prepared by spagyric processes.

Uses [Application of this homeopathic remedy for the designated usage is exclusively based on homeopathic experience. These "Uses" have not been evaluated by the Food and Drug Administration. With severe forms of this disease, a clinically proven therapy is indicated.]

For relief of minor sports injuries, including muscle strains, joint pain, sprains, and bruises

Warnings

For external use only. Do not use on open wounds! If symptoms persist, contact a licensed practitioner. If you have known sensitivity to any of the ingredients, please consult your licensed practitioner before use. If you are pregnant or nursing a baby, seek the advice of a health care professional before use.

Keep out of the reach of children.

Directions

Unless otherwise prescribed, apply a moderate amount of ointment 2 to 3 times per day by rubbing gently into the affected area.

Other information

Protect from light and heat.

Tamper Evident

Do not use this product if tamper evident strip is broken or removed from base of cap.

Inactive ingredients

Purified water, cetyl alcohol, cetylstearyl alcohol, synthetic cetaceum, triglycerides.

Manufactured by:
PEKANA® GmbH
D-88353 Kisslegg

Distributed by:
BioResource Inc.
Cotati, CA 94931

PRINCIPAL DISPLAY PANEL - 100 g Tube Box

INFLAMYAR™
Homeopathic Ointment

Relieves minor sports injuries including
> muscle strains > joint pain > sprains > bruises

3.5 OZ
100 g

PEKANA®